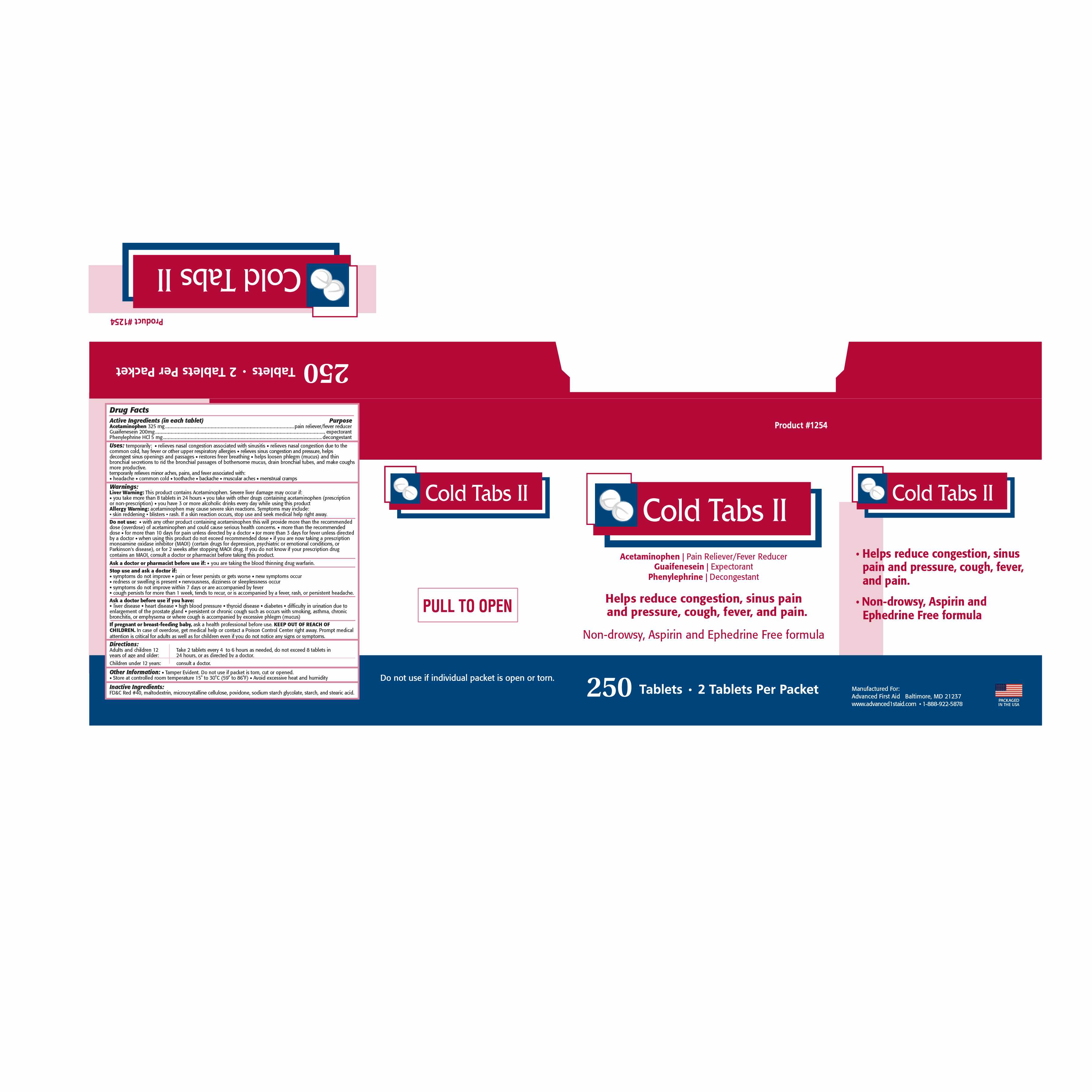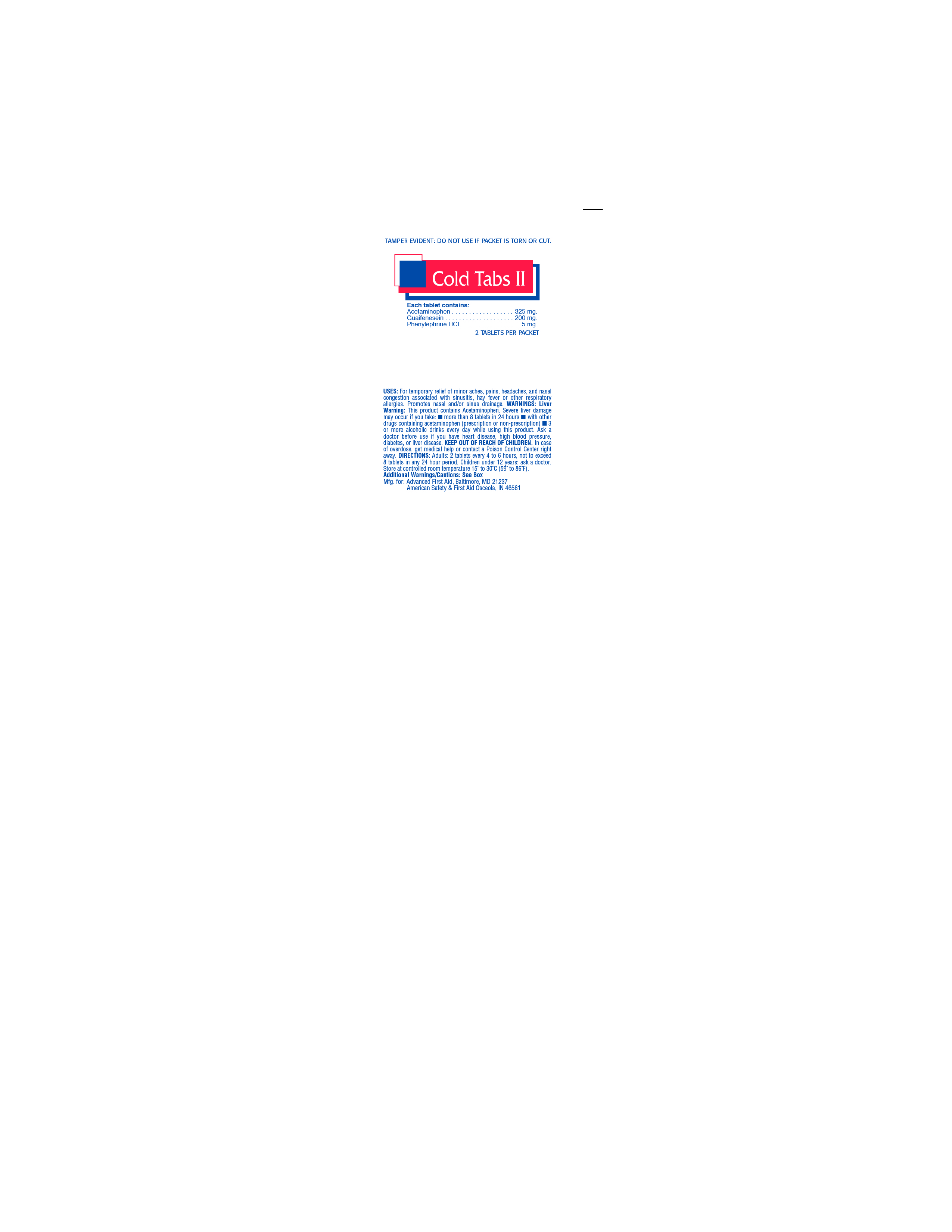 DRUG LABEL: COLD TABS II
NDC: 67060-106 | Form: TABLET
Manufacturer: ADVANCED FIRST AID, INC.
Category: otc | Type: HUMAN OTC DRUG LABEL
Date: 20161025

ACTIVE INGREDIENTS: ACETAMINOPHEN 325 1/1 1; GUAIFENESIN 200 1/1 1; PHENYLEPHRINE HYDROCHLORIDE 5 1/1 1
INACTIVE INGREDIENTS: FD&C RED NO. 40; CELLULOSE, MICROCRYSTALLINE; POVIDONE; SODIUM STARCH GLYCOLATE TYPE A CORN; STARCH, CORN; STEARIC ACID

ACTIVE INGREDIENT IN EACH TABLET-

Acetaminophen 325 mg

Guaifenesein 200 mg

Phenylephrine HCl 5 mg

PURPOSE

pain reliever/fever reducer

expectorant

decongestant

INDICATIONS AND USAGE

Uses: temporarily: • relieves nasal congestion associated with sinusitis • relieves nasal congestion due to the common cold, hay fever or other upper respiratory allergies • relieves sinus congestion and pressure, helps decongest sinus openings and passages • restores free breathing • helps loosen phlegm (mucus) and thin bronchial secretions to rid the bronchial passages of bothersome mucus, drain bronchial tubes, and make coughs more productive. temporarily relieves minor aches, pains, and fever associated with: • headache • common cold • toothache • backache • muscular aches • menstrual cramps

Warnings:

Liver Warning: This product contains Acetaminophen. Severe liver damage may occur if: • you take more than 8 tablets in 24 hours • you take with other drugs containing acetaminophen (prescription or non-prescription) • you have 3 or more alcoholic drinks every day while using this product

Do not use: • with any other product containing acetaminophen this will provide more than the recommended dose (overdose) of acetaminophen and could cause serious health concerns. • more than the recommended dose • for more than 10 days for pain unless directed by a doctor • for more than 3 days for fever unless directed by a doctor • when using this product do not exceed recommended dose • if you are now taking a prescription monoamine oxidase inhibitor (MAOI) (certain drugs for depression, psychiatric or emotional conditions, or Parkinson's disease), or for 2 weeks after stopping MAOI drug. If you do not know if your prescription drug contains an MAOI, consult a doctor or pharmacist before

taking this product.

Stop use and ask a doctor if: • symptoms do not improve • pain or fever persists or gets worse • new symptoms occur • redness or swelling is present • nervousness, dizziness or sleeplessness occur • symptoms do not improve within 7 days or are accompanied by fever cough persists for more than 1 week, tends to recur, or is accompanied by a fever, rash, or persistent headache.

Ask a doctor before use if you have: • heart disease • high blood pressure • thyroid disease • diabetes • difficulty in urination due to enlargement of the prostate gland • persistent or chronic cough such as occurs with smoking, asthma, chronic bronchitis, or emphysema or where cough is accompanied by excessive phlegm (mucus)

PREGNANCY OR BREAST FEEDING

If pregnant or breast-feeding baby, ask a health professional before use.

KEEP OUT OF REACH OF CHILDREN. In case of overdose, get medical help or contact a Poison Control Center right away. Prompt medical attention is critical for adults as well as for children even if you do not notice any signs or symptoms.

Directions:

Adults and children 12 years of age and older: Take 2 tablets every 4 to 6 hours or as needed, do not exceed 8 tablets in 24 hours, or asdirected by a doctor.

Children under 12 years: Consult a doctor.

INACTIVE INGREDIENT

Inactive Ingredients: FD&C Red #40, microcrystalline cellulose, povidone, sodium starch glycolate, starch, and stearic acid.